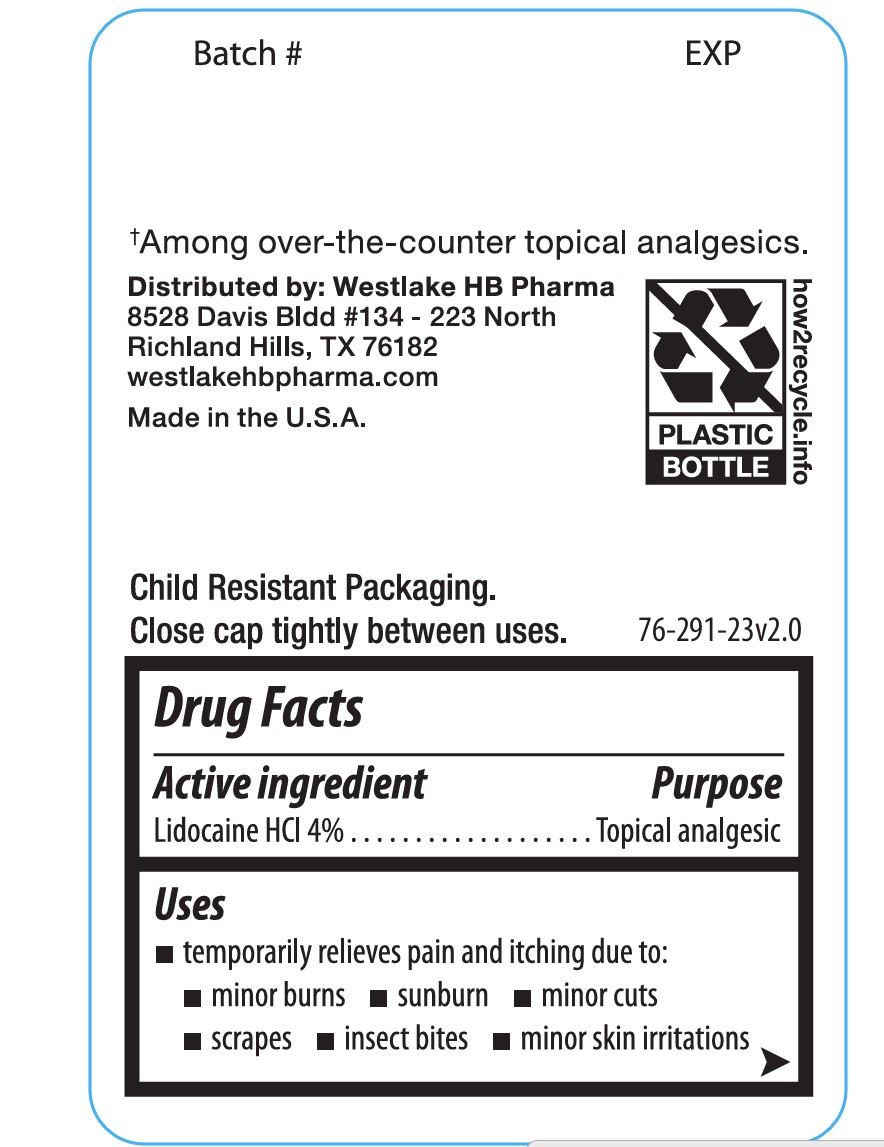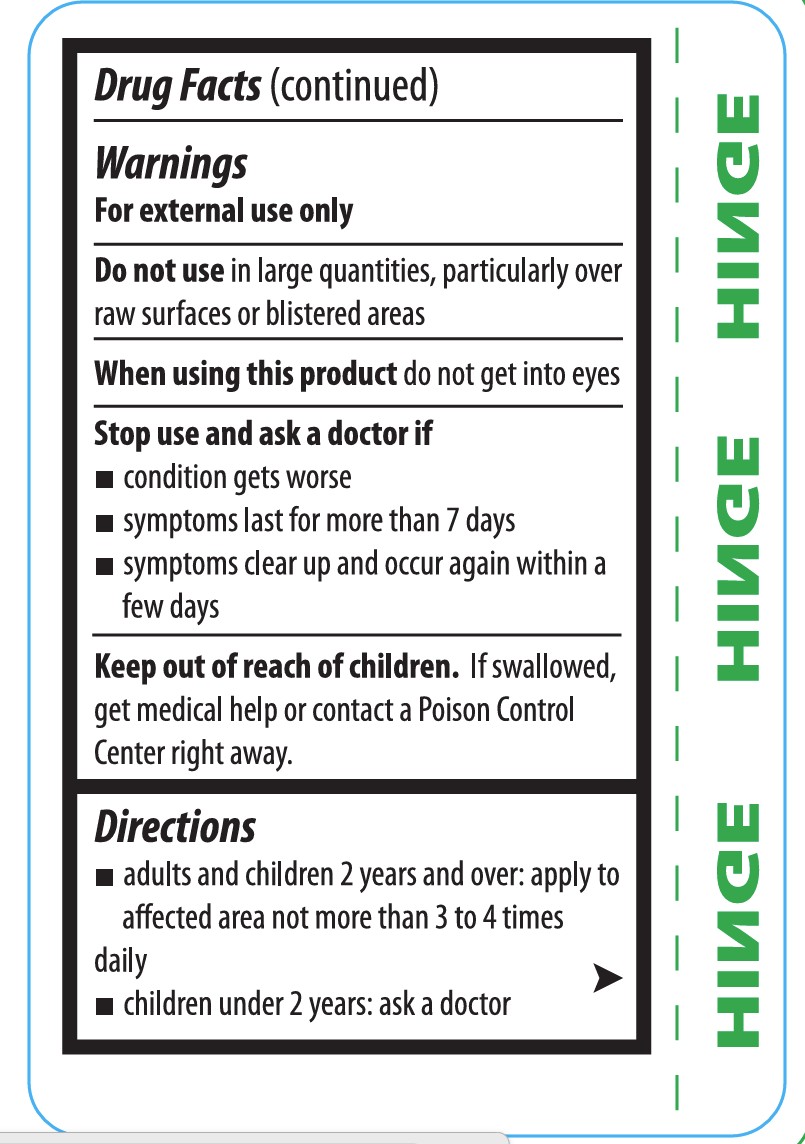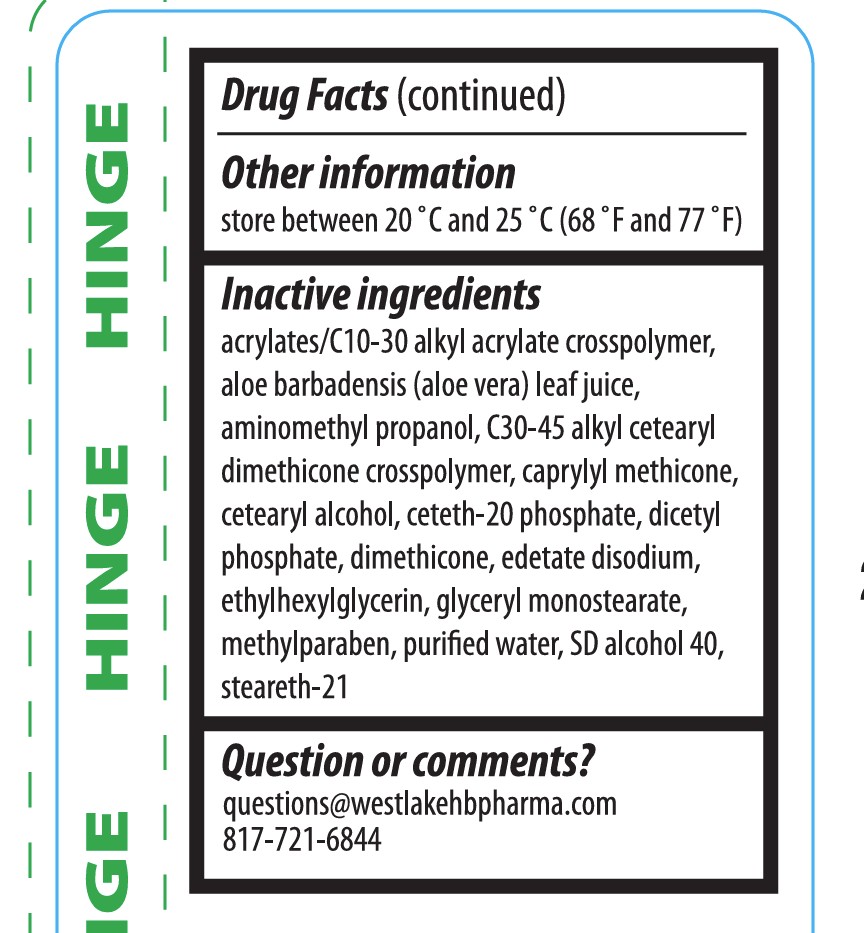 DRUG LABEL: Westlake Outdoor Pain and Itch Relieving
NDC: 82895-718 | Form: CREAM
Manufacturer: WESTLAKE HB PHARMA
Category: otc | Type: HUMAN OTC DRUG LABEL
Date: 20250701

ACTIVE INGREDIENTS: LIDOCAINE HYDROCHLORIDE 40 mg/1 g
INACTIVE INGREDIENTS: EDETATE DISODIUM ANHYDROUS; CETETH-20 PHOSPHATE; GLYCERYL STEARATE; AMINOMETHYL PROPANOL; ETHYLHEXYLGLYCERIN; CAPRYLYL METHICONE; STEARETH-21; DIMETHICONE 350; ALCOHOL; METHYLPARABEN; CETEARYL ALCOHOL; C30-45 ALKYL CETEARYL DIMETHICONE CROSSPOLYMER; ALOE BARBADENSIS LEAF JUICE; ACRYLATES/C10-30 ALKYL ACRYLATE CROSSPOLYMER (60000 MPA.S); WATER

Westlake Outdoor Pain Relieving Cream

PURPOSE

Topical analgesic

ACTIVE INGREDIENT

Lidocaine HCl 4%

ASK DOCTOR

- Condition gets worse
- symptoms last for more than 7 days
- symptoms clear up and occur again within a few days

DO NOT USE

- in large quantities, particularly over raw surface or blistered areas

KEEP OUT OF REACH OF CHILDREN

If swallowed get medical help or contact a Poison Control Center right away.

questions@westlakepharma.com

817-721-6844

WARNINGS

For external use onlyy

INSTRUCTIONS FOR USE

- adults and children 2 years and over: apply to affected area not more than 3 to 4 times daily
- children under 2 years: ask a doctor

STORAGE AND HANDLING

store between 20ºC and 25ºC (68ºF and 77ºF)

WHEN USING

do not get into eyes

INDICATIONS AND USAGE

- temporarily relieves pain and itching due to:
  - minor burns
  - sun burns
  - minor cuts
  - scrapes
  - insect bite
  - minor skin irritations

DOSAGE AND ADMINISTRATION

apply to affected area not more than 3 to 4 times daily

INACTIVE INGREDIENT

acrylates/C10-30 alkyl acrylate crosspolymer, aloe barbadensis (aleo vera) leaf juice, aminomethyl propanol, C30-45 alkyl cetearyl dimethicone crosspolymer, caprylyl methicone, cetearyl alcohol, ceteth-30 phosphate, dicetyl phoshpate, dimethicone, edetate disodium, ethylhexylglycerin, glyceryl monosterate, methylparaben, purified water, SD alcohol 40, steareth-21